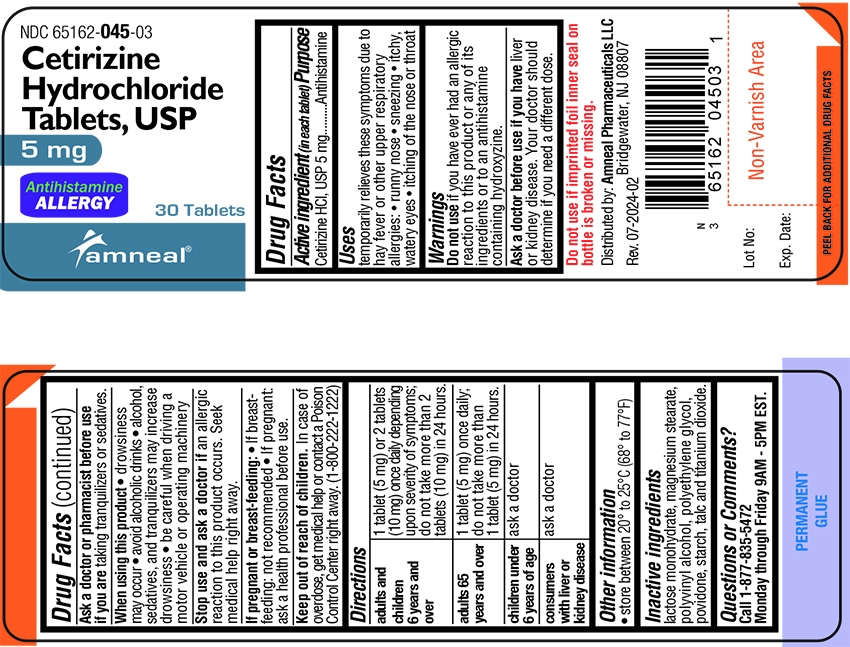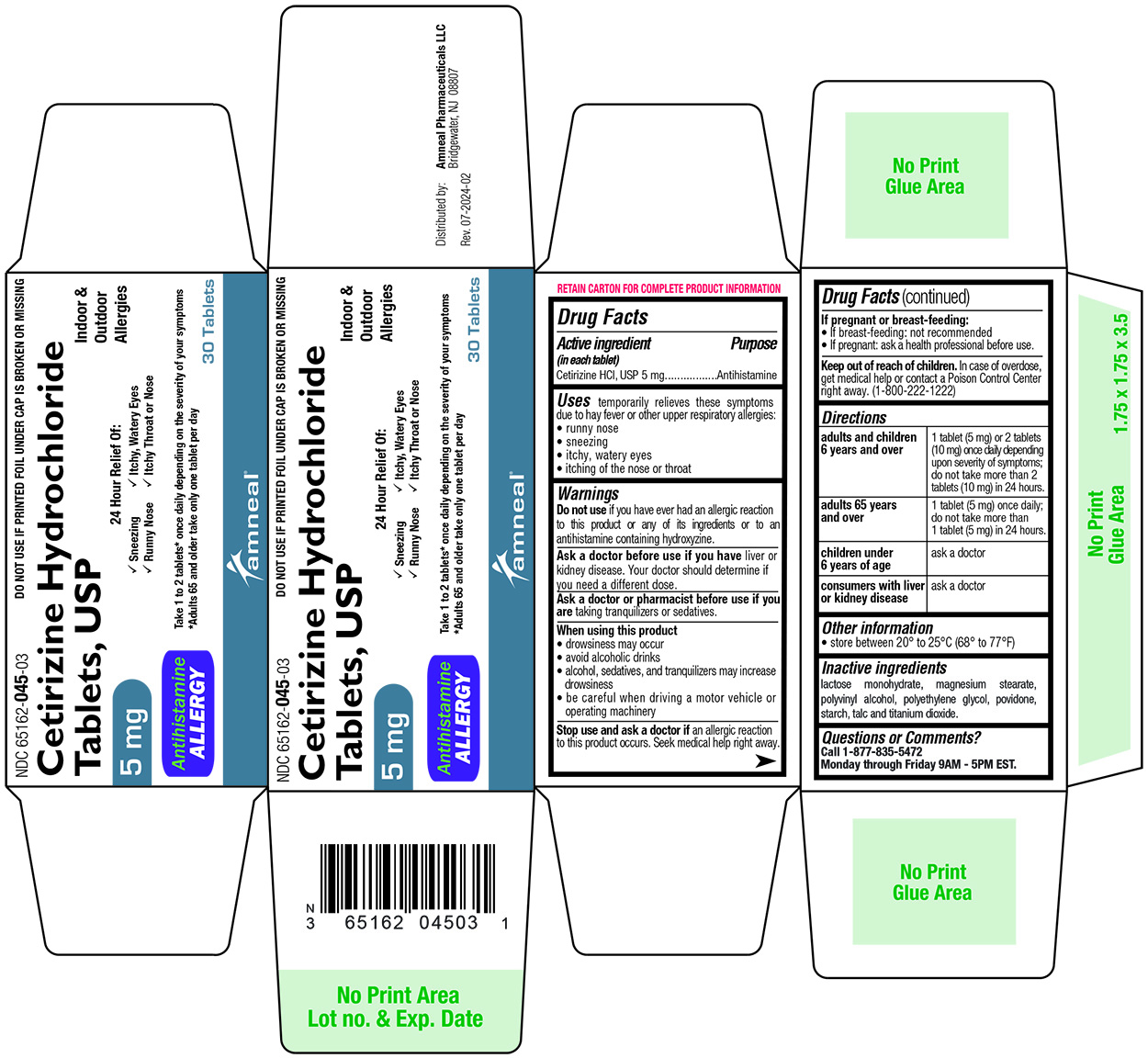 DRUG LABEL: Cetirizine Hydrochloride
NDC: 65162-045 | Form: TABLET
Manufacturer: Amneal Pharmaceuticals LLC
Category: otc | Type: HUMAN OTC DRUG LABEL
Date: 20240731

ACTIVE INGREDIENTS: CETIRIZINE HYDROCHLORIDE 5 mg/1 1
INACTIVE INGREDIENTS: LACTOSE MONOHYDRATE; MAGNESIUM STEARATE; POLYVINYL ALCOHOL, UNSPECIFIED; POLYETHYLENE GLYCOL, UNSPECIFIED; POVIDONE; STARCH, CORN; TALC; TITANIUM DIOXIDE

CETIRIZINE HYDROCHLORIDE TABLETS

Drug Facts

ACTIVE INGREDIENT

(in each tablet)

Cetirizine HCl, USP 5 mg

PURPOSE

Antihistamine

INDICATIONS AND USAGE

temporarily relieves these symptoms due to hay fever or other upper respiratory allergies:

● runny nose

● sneezing

● itchy, watery eyes

● itching of the nose or throat

WARNINGS

Do not use if you have ever had an allergic reaction to this product or any of its ingredients or to an antihistamine containing hydroxyzine.

ASK DOCTOR

Ask a doctor before use if you have liver or kidney disease. Your doctor should determine if you need a different dose.

ASK DOCTOR/PHARMACIST

Ask a doctor or pharmacist before use if you are taking tranquilizers or sedatives.

When using this product

● drowsiness may occur

● avoid alcoholic drinks

● alcohol, sedatives, and tranquilizers may increase drowsiness

● be careful when driving a motor vehicle or operating machinery

STOP USE

Stop use and ask a doctor if an allergic reaction to this product occurs. Seek medical help right away.

PREGNANCY OR BREAST FEEDING

If pregnant or breast-feeding :

• if breast-feeding: not recommended

• if pregnant: ask a health professional before use.

Keep out of reach of children. In case of overdose, get medical help or contact a Poison Control Center right away. (1-800-222-1222)

DIRECTIONS

Adults and children 6 years and over | 1 tablet (5 mg) or 2 tablets (10 mg) once daily depending upon severity of symptoms; do not take more than 2 tablets (10 mg) in 24 hours.
Adults 65 years and over | 1 tablet (5 mg) once daily; do not take more than 1 tablet (5 mg) in 24 hours.
Children under 6 years of age | ask a doctor
Consumers with liver or kidney disease | ask a doctor

OTHER INFORMATION

• store between 20° to 25°C (68° to 77°F)

INACTIVE INGREDIENTS

lactose monohydrate, magnesium stearate, polyvinyl alcohol, polyethylene glycol, povidone, starch, talc and titanium dioxide.

OTC - QUESTIONS

Questions or Comments?

Call 1-877-835-5472

Monday through Friday 9AM - 5PM EST.

Distributed by:
Amneal Pharmaceuticals LLC
Bridgewater, NJ08807

Rev. 07-2024-02